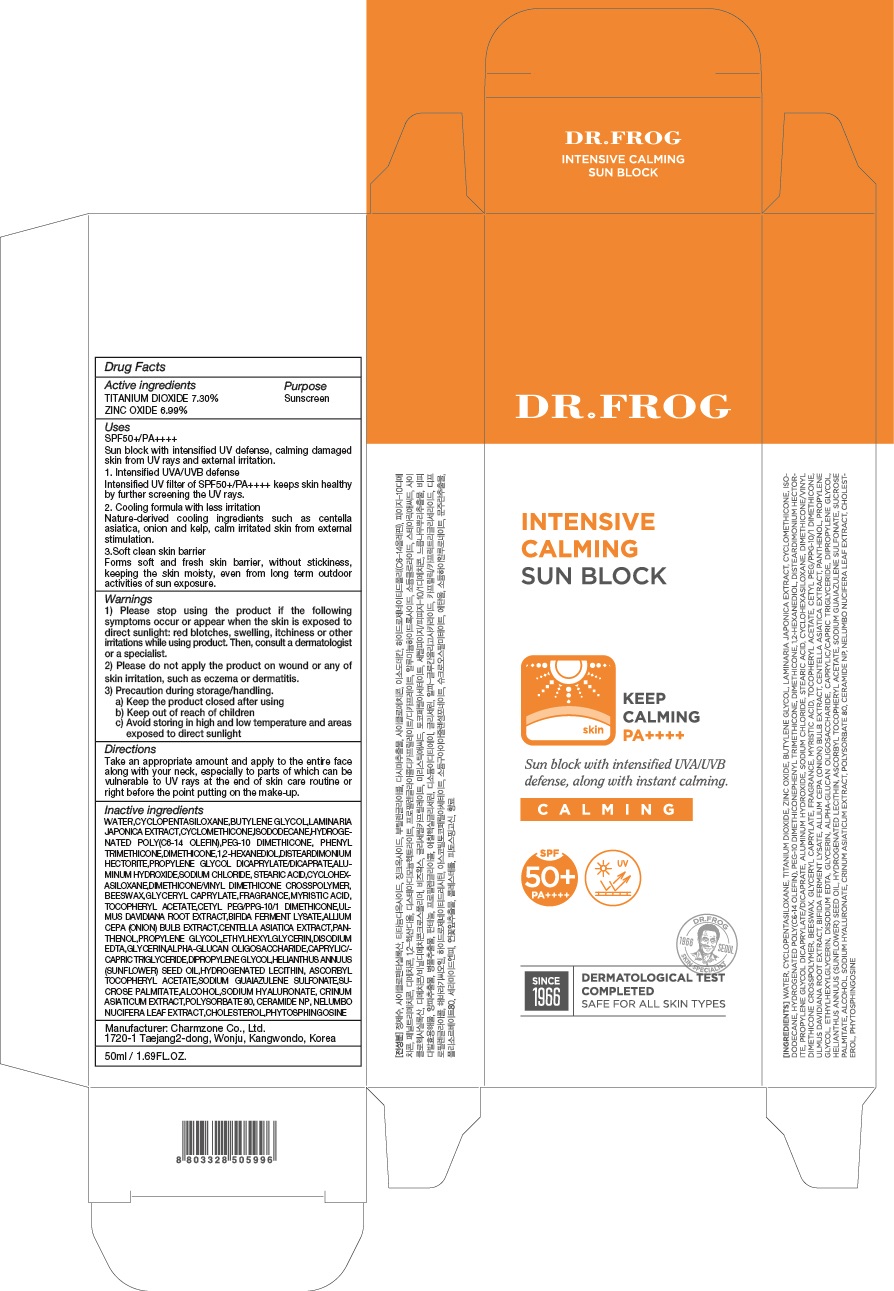 DRUG LABEL: DR FROG INTENSIVE CALMING SUN BLOCK
NDC: 22201-1030 | Form: CREAM
Manufacturer: Charmzone Co Ltd
Category: otc | Type: HUMAN OTC DRUG LABEL
Date: 20180413

ACTIVE INGREDIENTS: TITANIUM DIOXIDE 3.65 g/50 mL; ZINC OXIDE 3.49 g/50 mL
INACTIVE INGREDIENTS: WATER; BUTYLENE GLYCOL

ACTIVE INGREDIENT

Active ingredients: TITANIUM DIOXIDE 7.30%, ZINC OXIDE 6.99%

INACTIVE INGREDIENT

Inactive ingredients:

WATER,CYCLOPENTASILOXANE,BUTYLENE GLYCOL,LAMINARIA JAPONICA EXTRACT,CYCLOMETHICONE,ISODODECANE,HYDROGENATED POLY(C6-14 OLEFIN),PEG-10 DIMETHICONE,PHENYL TRIMETHICONE,DIMETHICONE,1,2-HEXANEDIOL,DISTEARDIMONIUM HECTORITE,PROPYLENE GLYCOL DICAPRYLATE/DICAPRATE,ALUMINUM HYDROXIDE,SODIUM CHLORIDE,STEARIC ACID,CYCLOHEXASILOXANE,DIMETHICONE/VINYL DIMETHICONE CROSSPOLYMER,BEESWAX,GLYCERYL CAPRYLATE,FRAGRANCE,MYRISTIC ACID,TOCOPHERYL ACETATE,CETYL PEG/PPG-10/1 DIMETHICONE,ULMUS DAVIDIANA ROOT EXTRACT,BIFIDA FERMENT LYSATE,ALLIUM CEPA (ONION) BULB EXTRACT,CENTELLA ASIATICA EXTRACT,PANTHENOL,PROPYLENE GLYCOL,ETHYLHEXYLGLYCERIN,DISODIUM EDTA,GLYCERIN,ALPHA-GLUCAN OLIGOSACCHARIDE,CAPRYLIC/CAPRIC TRIGLYCERIDE,DIPROPYLENE GLYCOL,HELIANTHUS ANNUUS (SUNFLOWER) SEED OIL,HYDROGENATED LECITHIN,ASCORBYL TOCOPHERYL ACETATE,SODIUM GUAIAZULENE SULFONATE,SUCROSE PALMITATE,ALCOHOL,SODIUM HYALURONATE,CRINUM ASIATICUM EXTRACT,POLYSORBATE 80,CERAMIDE NP,NELUMBO NUCIFERA LEAF EXTRACT,CHOLESTEROL,PHYTOSPHINGOSINE

PURPOSE

Purpose: Sunscreen

WARNINGS

1) Please stop using the product if the following symptoms occur or appear when the skin is exposed to direct sunlight: red blotches, swelling, itchiness or other irritations while using product. Then, consult a dermatologist or a specialist.

2) Please do not apply the product on wound or any of skin irritation, such as eczema or dermatitis.

3) Precaution during storage/handling. a) Keep the product closed after using b) Keep out of reach of children c) Avoid storing in high and low temperature and areas exposed to direct sunlight

DESCRIPTION

Uses:

[UV PROTECTION]

SPF50+/PA++++

Sun block with intensified UV defense, calming damaged skin from UV rays and external irritation.

1. Intensified UVA/UVB defense Intensified UV filter of SPF50+/PA++++ keeps skin healthy by further screening the UV rays.

2. Cooling formula with less irritation Nature-derived cooling ingredients such as centella asiatica, onion and kelp, calm irritated skin from external stimulation.

3.Soft clean skin barrier Forms soft and fresh skin barrier, without stickiness, keeping the skin moisty, even from long term outdoor activities of sun exposure.

Directions:

Take an appropriate amount and apply to the entire face along with your neck, especially to parts of which can be vulnerable to UV rays at the end of skin care routine or right before the point putting on the make-up.